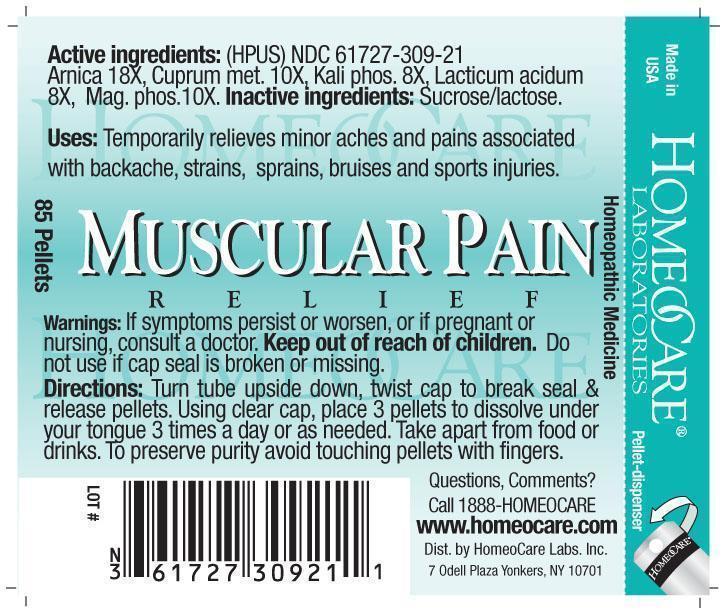 DRUG LABEL: Muscular Pain Relief
NDC: 61727-309 | Form: PELLET
Manufacturer: Homeocare Laboratories
Category: homeopathic | Type: HUMAN OTC DRUG LABEL
Date: 20181226

ACTIVE INGREDIENTS: ARNICA MONTANA 18 [hp_X]/4 g; COPPER 10 [hp_X]/4 g; POTASSIUM PHOSPHATE, DIBASIC 8 [hp_X]/4 g; LACTIC ACID, DL- 8 [hp_X]/4 g; MAGNESIUM PHOSPHATE, DIBASIC TRIHYDRATE 10 [hp_X]/4 g
INACTIVE INGREDIENTS: SUCROSE; LACTOSE

Muscular Pain Relief

Active ingredients:

Arnica 18X, Cuprum met. 10X, Kali phos. 8X, Lacticum acidum 8X, Mag. phos. 10X.

Inactive ingredients:

Sucrose/lactose.

Purpose:

Temporarily relieves minor aches and pains associated with backache, strains, sprains, bruises, and sports injuries.

Keep out of reach of children.

Warnings:

If symptoms persist or worsen, or if pregnant or nursing, consult a doctor. Keep out of reach of children. Do not use if cap seal is broken or missing.

Indications & Usage:

Turn tube upside down, twist cap to break seal & release pellets. Using clear cap, place 3 pellets to dissolve under your tongue 3 times a day or as needed. Take apart from food or drinks. To preserve purity avoid touching pellets with fingers.

Dosage & Administration:

Turn tube upside down, twist cap to break seal & release pellets. Using clear cap, place 3 pellets to dissolve under your tongue 3 times a day or as needed. Take apart from food or drinks. To preserve purity avoid touching pellets with fingers.

Muscular Pain Relief

Homeopathic Medicine

85 Pellets

hcl_label_musc. pain.jpg